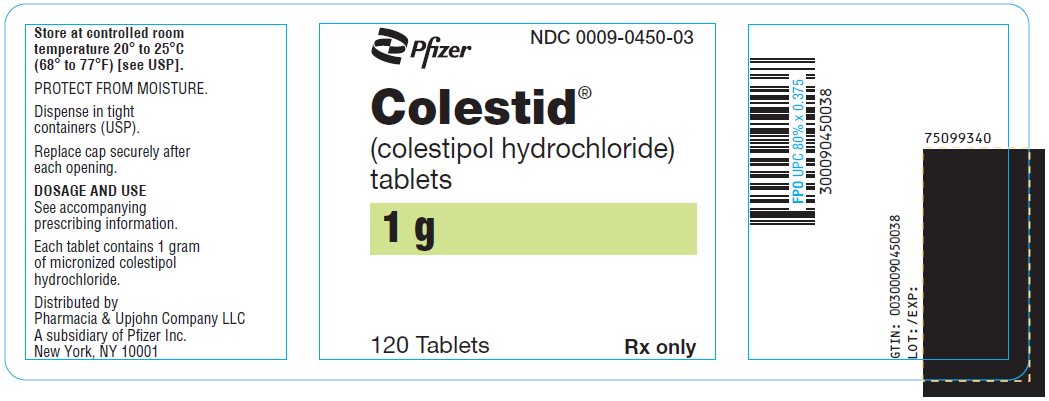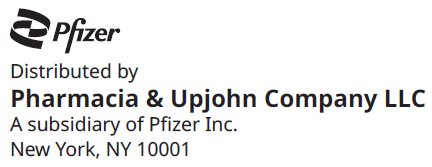 DRUG LABEL: Colestid
NDC: 0009-0450 | Form: TABLET
Manufacturer: Pharmacia & Upjohn Company LLC
Category: prescription | Type: HUMAN PRESCRIPTION DRUG LABEL
Date: 20241024

ACTIVE INGREDIENTS: COLESTIPOL HYDROCHLORIDE 1 g/1 1
INACTIVE INGREDIENTS: TRIACETIN; CARNAUBA WAX; HYPROMELLOSE, UNSPECIFIED; MAGNESIUM STEARATE; POVIDONE, UNSPECIFIED; SILICON DIOXIDE

Colestid®
colestipol hydrochloride tablets

DESCRIPTION

The active ingredient in COLESTID Tablets is micronized colestipol hydrochloride, which is a lipid lowering agent for oral use. Colestipol is an insoluble, high molecular weight basic anion-exchange copolymer of diethylenetriamine and 1-chloro-2, 3-epoxypropane, with approximately 1 out of 5 amine nitrogens protonated (chloride form). It is a light yellow water-insoluble resin which is hygroscopic and swells when suspended in water or aqueous fluids.

Each COLESTID Tablet contains one gram of micronized colestipol hydrochloride. COLESTID Tablets are light yellow in color and are tasteless and odorless. Inactive ingredients: cellulose acetate phthalate, glyceryl triacetate, carnauba wax, hypromellose, magnesium stearate, povidone, silicon dioxide. COLESTID Tablets contain no calories.

CLINICAL PHARMACOLOGY

Cholesterol is the major, and probably the sole precursor of bile acids. During normal digestion, bile acids are secreted via the bile from the liver and gall bladder into the intestines. Bile acids emulsify the fat and lipid materials present in food, thus facilitating absorption. A major portion of the bile acids secreted is reabsorbed from the intestines and returned via the portal circulation to the liver, thus completing the enterohepatic cycle. Only very small amounts of bile acids are found in normal serum.

Colestipol hydrochloride binds bile acids in the intestine forming a complex that is excreted in the feces. This nonsystemic action results in a partial removal of the bile acids from the enterohepatic circulation, preventing their reabsorption. Since colestipol hydrochloride is an anion exchange resin, the chloride anions of the resin can be replaced by other anions, usually those with a greater affinity for the resin than the chloride ion.

Colestipol hydrochloride is hydrophilic, but it is virtually water insoluble (99.75%) and it is not hydrolyzed by digestive enzymes. The high molecular weight polymer in colestipol hydrochloride apparently is not absorbed. In humans, less than 0.17% of a single ^14C-labeled colestipol hydrochloride dose is excreted in the urine when given following 60 days of dosing of 20 grams of colestipol hydrochloride per day.

The increased fecal loss of bile acids due to colestipol hydrochloride administration leads to an increased oxidation of cholesterol to bile acids. This results in an increase in the number of low-density lipoprotein (LDL) receptors, increased hepatic uptake of LDL and a decrease in beta lipoprotein or LDL serum levels, and a decrease in serum cholesterol levels. Although colestipol hydrochloride produces an increase in the hepatic synthesis of cholesterol in man, serum cholesterol levels fall.

There is evidence to show that this fall in cholesterol is secondary to an increased rate of clearance of cholesterol-rich lipoproteins (beta or low-density lipoproteins) from the plasma. Serum triglyceride levels may increase or remain unchanged in colestipol hydrochloride treated patients.

The decline in serum cholesterol levels with colestipol hydrochloride treatment is usually evident by one month. When colestipol hydrochloride is discontinued, serum cholesterol levels usually return to baseline levels within one month. Periodic determinations of serum cholesterol levels as outlined in the National Cholesterol Education Program (NCEP) guidelines, should be done to confirm a favorable initial and long-term response.^1

In a large, placebo-controlled, multiclinic study, the LRC-CPPT^2, hypercholesterolemic subjects treated with cholestyramine, a bile-acid sequestrant with a mechanism of action and an effect on serum cholesterol similar to that of colestipol hydrochloride, had reductions in total and LDL-C. Over the 7-year study period the cholestyramine group experienced a 19% reduction (relative to the incidence in the placebo group) in the combined rate of coronary heart disease (CHD) death plus nonfatal myocardial infarction (cumulative incidences of 7% cholestyramine and 8.6% placebo). The subjects included in the study were middle-aged men (aged 35–59) with serum cholesterol levels above 265 mg/dL, LDL-C above 175 mg/dL on a moderate cholesterol-lowering diet, and no history of heart disease. It is not clear to what extent these findings can be extrapolated to other segments of the hypercholesterolemic population not studied.

Treatment with colestipol results in a significant increase in lipoprotein LpAI. Lipoprotein LpAI is one of the two major lipoprotein particles within the high-density lipoprotein (HDL) density range^3, and has been shown in cell culture to promote cholesterol efflux or removal from cells^4. Although the significance of this finding has not been established in clinical studies, the elevation of the lipoprotein LpAI particle within the HDL fraction is consistent with an antiatherogenic effect of colestipol hydrochloride, even though little change is observed in HDL cholesterol (HDL-C).

In patients with heterozygous familial hypercholesterolemia who have not obtained an optimal response to colestipol hydrochloride alone in maximal doses, the combination of colestipol hydrochloride and nicotinic acid has been shown to further lower serum cholesterol, triglyceride, and LDL-cholesterol (LDL-C) values. Simultaneously, HDL-C values increased significantly. In many such patients it is possible to normalize serum lipid values.^5–7

Preliminary evidence suggests that the cholesterol-lowering effects of lovastatin and the bile acid sequestrant, colestipol hydrochloride, are additive.

The effect of intensive lipid-lowering therapy on coronary atherosclerosis has been assessed by arteriography in hyperlipidemic patients. In these randomized, controlled clinical trials, patients were treated for two to four years by either conventional measures (diet, placebo, or in some cases low-dose resin), or with intensive combination therapy using diet and COLESTID Granules plus either nicotinic acid or lovastatin. When compared to conventional measures, intensive lipid-lowering combination therapy significantly reduced the frequency of progression and increased the frequency of regression of coronary atherosclerotic lesions in patients with or at risk for coronary artery disease.^8–11

INDICATIONS AND USAGE

Since no drug is innocuous, strict attention should be paid to the indications and contraindications, particularly when selecting drugs for chronic long-term use.

COLESTID Tablets are indicated as adjunctive therapy to diet for the reduction of elevated serum total and LDL-C in patients with primary hypercholesterolemia (elevated LDL-C) who do not respond adequately to diet. Generally, COLESTID Tablets have no clinically significant effect on serum triglycerides, but with their use, triglyceride levels may be raised in some patients.

Therapy with lipid-altering agents should be a component of multiple risk factor intervention in those individuals at significantly increased risk for atherosclerotic vascular disease due to hypercholesterolemia. Treatment should begin and continue with dietary therapy (see NCEP guidelines). A minimum of six months of intensive dietary therapy and counseling should be carried out prior to initiation of drug therapy. Shorter periods may be considered in patients with severe elevations of LDL-C or with definite CHD.

According to the NCEP guidelines, the goal of treatment is to lower LDL-C, and LDL-C is to be used to initiate and assess treatment response. Only if LDL-C levels are not available, should the Total-C be used to monitor therapy. The NCEP treatment guidelines are shown below.

 |  | LDL-Cholesterol mg/dL (mmol/L)
Definite Atherosclerotic Disease [Coronary heart disease or peripheral vascular disease (including symptomatic carotid artery disease).] | Two or More Other Risk Factors [Other risk factors for coronary heart disease (CHD) include: age (males: ≥45 years; female: ≥55 years or premature menopause without estrogen replacement therapy); family history of premature CHD; current cigarette smoking; hypertension; confirmed HDL-C <35 mg/dL (0.91 mmol/L); and diabetes mellitus. Subtract one risk factor if HDL-C is ≥60 mg/dL (1.6 mmol/L).] | Initiation Level | Goal
No | No | ≥190 (≥4.9) | <160 (<4.1)
No | Yes | ≥160 (≥4.1) | <130 (<3.4)
Yes | Yes or No | ≥130 (≥3.4) | ≤100 (≤2.6)

CONTRAINDICATIONS

COLESTID Tablets are contraindicated in those individuals who have shown hypersensitivity to any of their components.

PRECAUTIONS

Prior to initiating therapy with COLESTID Tablets, secondary causes of hypercholesterolemia (e.g., poorly controlled diabetes mellitus, hypothyroidism, nephrotic syndrome, dysproteinemias, obstructive liver disease, other drug therapy, alcoholism), should be excluded, and a lipid profile performed to assess total cholesterol, HDL-C, and triglycerides (TG). For individuals with TG less than 400 mg/dL (<4.5 mmol/L), LDL-C can be estimated using the following equation:

LDL-C = Total cholesterol − [(Triglycerides/5) + HDL-C]

For TG levels >400 mg/dL, this equation is less accurate and LDL-C concentrations should be determined by ultracentrifugation. In hypertriglyceridemic patients, LDL-C may be low or normal despite elevated Total-C. In such cases COLESTID Tablets may not be indicated.

Because it sequesters bile acids, colestipol hydrochloride may interfere with normal fat absorption and, thus, may reduce absorption of folic acid and fat soluble vitamins such as A, D, and K.

Chronic use of colestipol hydrochloride may be associated with an increased bleeding tendency due to hypoprothrombinemia from vitamin K deficiency. This will usually respond promptly to parenteral vitamin K1 and recurrences can be prevented by oral administration of vitamin K1.

Serum cholesterol and triglyceride levels should be determined periodically based on NCEP guidelines to confirm a favorable initial and adequate long-term response.

COLESTID Tablets may produce or severely worsen pre-existing constipation. The dosage should be increased gradually in patients to minimize the risk of developing fecal impaction. In patients with pre-existing constipation, the starting dose should be 2 grams once or twice a day. Increased fluid and fiber intake should be encouraged to alleviate constipation and a stool softener may occasionally be indicated. If the initial dose is well tolerated, the dose may be increased as needed by a further 2 to 4 grams/day (at monthly intervals) with periodic monitoring of serum lipoproteins. If constipation worsens or the desired therapeutic response is not achieved at 2 to 16 grams/day, combination therapy or alternate therapy should be considered. Particular effort should be made to avoid constipation in patients with symptomatic coronary artery disease. Constipation associated with COLESTID Tablets may aggravate hemorrhoids.

While there have been no reports of hypothyroidism induced in individuals with normal thyroid function, the theoretical possibility exists, particularly in patients with limited thyroid reserve.

Since colestipol hydrochloride is a chloride form of an anion exchange resin, there is a possibility that prolonged use may lead to the development of hyperchloremia acidosis.

Carcinogenesis, Mutagenesis and Impairment of Fertility

In studies conducted in rats in which cholestyramine resin (a bile acid sequestering agent similar to colestipol hydrochloride) was used as a tool to investigate the role of various intestinal factors, such as fat, bile salts, and microbial flora, in the development of intestinal tumors induced by potent carcinogens, the incidence of such tumors was observed to be greater in cholestyramine resin treated rats than in control rats.

The relevance of this laboratory observation from studies in rats with cholestyramine resin to the clinical use of COLESTID Tablets is not known. In the LRC-CPPT study referred to above, the total incidence of fatal and nonfatal neoplasms was similar in both treatment groups. When the many different categories of tumors are examined, various alimentary system cancers were somewhat more prevalent in the cholestyramine group. The small numbers and the multiple categories prevent conclusions from being drawn. Further follow-up of the LRC-CPPT participants by the sponsors of that study is planned for cause-specific mortality and cancer morbidity. When colestipol hydrochloride was administered in the diet to rats for 18 months, there was no evidence of any drug related intestinal tumor formation. In the Ames assay, colestipol hydrochloride was not mutagenic.

Use in Pregnancy

Since colestipol hydrochloride is essentially not absorbed systemically (less than 0.17% of the dose), it is not expected to cause fetal harm when administered during pregnancy in recommended dosages. There are no adequate and well-controlled studies in pregnant women, and the known interference with absorption of fat-soluble vitamins may be detrimental even in the presence of supplementation. The use of COLESTID tablets in pregnancy or by women of childbearing potential requires that the potential benefits of drug therapy be weighed against possible hazards to the mother or child.

Nursing Mothers

Caution should be exercised when COLESTID Tablets are administered to a nursing mother. The possible lack of proper vitamin absorption described in the "Pregnancy" section may have an effect on nursing infants.

Pediatric Use

Safety and effectiveness in the pediatric population have not been established.

Information for Patients

COLESTID Tablets may be larger than pills you have taken before. If you have had swallowing problems or choking with food, liquids or other tablets or capsules in the past, you should discuss this with your doctor before taking COLESTID Tablets.

It is important that you take COLESTID Tablets correctly:

1. Always take one tablet at a time and swallow promptly.
2. Swallow each tablet whole. Do not cut, crush, or chew the tablets.
3. COLESTID Tablets must be taken with water or another liquid that you prefer. Swallowing the tablets will be easier if you drink plenty of liquid as you swallow each tablet.

Difficulty swallowing and temporary obstruction of the esophagus (the tube between your mouth and stomach) have been rarely reported in patients taking COLESTID Tablets. If a tablet does get stuck after you swallow it, you may notice pressure or discomfort. If this happens to you, you should contact your doctor. Do not take COLESTID Tablets again without your doctor's advice.

If you are taking other medications, you should take them at least one hour before or four hours after taking COLESTID Tablets.

DRUG INTERACTIONS

Since colestipol hydrochloride is an anion exchange resin, it may have a strong affinity for anions other than the bile acids. In vitro studies have indicated that colestipol hydrochloride binds a number of drugs. Therefore, COLESTID Tablets may delay or reduce the absorption of concomitant oral medication. The interval between the administration of COLESTID Tablets and any other medication should be as long as possible. Patients should take other drugs at least one hour before or four hours after COLESTID Tablets to avoid impeding their absorption.

Repeated doses of colestipol hydrochloride given prior to a single dose of propranolol in human trials have been reported to decrease propranolol absorption. However, in a follow-up study in normal subjects, single-dose administration of colestipol hydrochloride and propranolol and twice-a-day administration for 5 days of both agents did not affect the extent of propranolol absorption, but had a small yet statistically significant effect on its rate of absorption; the time to reach maximum concentration was delayed approximately 30 minutes. Effects on the absorption of other beta-blockers have not been determined. Therefore, patients on propranolol should be observed when COLESTID Tablets are either added or deleted from a therapeutic regimen.

Studies in humans show that the absorption of chlorothiazide as reflected in urinary excretion is markedly decreased even when administered one hour before colestipol hydrochloride. The absorption of tetracycline, furosemide, penicillin G, hydrochlorothiazide, and gemfibrozil was significantly decreased when given simultaneously with colestipol hydrochloride; these drugs were not tested to determine the effect of administration one hour before colestipol hydrochloride.

No depressant effect on blood levels in humans was noted when colestipol hydrochloride was administered with any of the following drugs: aspirin, clindamycin, clofibrate, methyldopa, nicotinic acid (niacin), tolbutamide, phenytoin or warfarin. Particular caution should be observed with digitalis preparations since there are conflicting results for the effect of colestipol hydrochloride on the availability of digoxin and digitoxin. The potential for binding of these drugs if given concomitantly is present. Discontinuing colestipol hydrochloride could pose a hazard to health if a potentially toxic drug that is significantly bound to the resin has been titrated to a maintenance level while the patient was taking colestipol hydrochloride.

Bile acid binding resins may also interfere with the absorption of oral phosphate supplements and hydrocortisone.

A study has shown that cholestyramine binds bile acids and reduces mycophenolic acid exposure. As colestipol also binds bile acids, colestipol may reduce mycophenolic acid exposure and potentially reduce efficacy of mycophenolate mofetil.

ADVERSE REACTIONS

Gastrointestinal

The most common adverse reactions are confined to the gastrointestinal tract. To achieve minimal GI disturbance with an optimal LDL-C lowering effect, a gradual increase of dosage starting with 2 grams, once or twice daily is recommended. Constipation is the major single complaint and at times is severe. Most instances of constipation are mild, transient, and controlled with standard treatment. Increased fluid intake and inclusion of additional dietary fiber should be the first step; a stool softener may be added if needed. Some patients require decreased dosage or discontinuation of therapy. Hemorrhoids may be aggravated.

Other, less frequent gastrointestinal complaints consist of abdominal discomfort (abdominal pain and cramping), intestinal gas (bloating and flatulence), indigestion and heartburn, diarrhea and loose stools, and nausea and vomiting. Bleeding hemorrhoids and blood in the stool have been infrequently reported. Peptic ulceration, cholecystitis, and cholelithiasis have been rarely reported in patients receiving colestipol hydrochloride granules, and are not necessarily drug related.

Difficulty swallowing and transient esophageal obstruction have been rarely reported in patients taking COLESTID Tablets.

Transient and modest elevations of aspartate aminotransferase (AST, SGOT), alanine aminotransferase (ALT, SGPT) and alkaline phosphatase were observed on one or more occasions in various patients treated with colestipol hydrochloride.

The following nongastrointestinal adverse reactions have been reported with generally equal frequency in patients receiving COLESTID Tablets, colestipol granules, or placebo in clinical studies:

Cardiovascular

Chest pain, angina, and tachycardia have been infrequently reported.

Hypersensitivity

Rash has been infrequently reported. Urticaria and dermatitis have been rarely noted in patients receiving colestipol hydrochloride granules.

Musculoskeletal

Musculoskeletal pain, aches and pains in the extremities, joint pain and arthritis, and backache have been reported.

Neurologic

Headache, migraine headache, and sinus headache have been reported. Other infrequently reported complaints include dizziness, light-headedness, and insomnia.

Miscellaneous

Anorexia, fatigue, weakness, shortness of breath, and swelling of the hands or feet, have been infrequently reported.

OVERDOSAGE

Overdosage of COLESTID Tablets has not been reported. Should overdosage occur, however, the chief potential harm would be obstruction of the gastrointestinal tract. The location of such potential obstruction, the degree of obstruction and the presence or absence of normal gut motility would determine treatment.

DOSAGE AND ADMINISTRATION

For adults, COLESTID Tablets are recommended in doses of 2 to 16 grams/day given once or in divided doses. The starting dose should be 2 grams once or twice daily. Dosage increases of 2 grams, once or twice daily should occur at 1- or 2-month intervals. Appropriate use of lipid profiles as per NCEP guidelines including LDL-C and triglycerides, is advised so that optimal but not excessive doses are used to obtain the desired therapeutic effect on LDL-C level. If the desired therapeutic effect is not obtained at a dose of 2 to 16 grams/day with good compliance and acceptable side effects, combined therapy or alternate treatment should be considered.

COLESTID Tablets must be taken one at a time and be promptly swallowed whole, using plenty of water or other appropriate liquid. Do not cut, crush, or chew the tablets. Patients should take other drugs at least one hour before or four hours after COLESTID Tablets to minimize possible interference with their absorption. (See DRUG INTERACTIONS.)

Before Administration of COLESTID Tablets

1. Define the type of hyperlipoproteinemia, as described in NCEP guidelines.
2. Institute a trial of diet and weight reduction.
3. Establish baseline serum total and LDL-C and triglyceride levels.

During Administration of COLESTID Tablets

1. The patient should be carefully monitored clinically, including serum cholesterol and triglyceride levels. Periodic determinations of serum cholesterol levels as outlined in the NCEP guidelines should be done to confirm a favorable initial and long-term response.
2. Failure of total or LDL-C to fall within the desired range should lead one to first examine dietary and drug compliance. If these are deemed acceptable, combined therapy or alternate treatment should be considered.
3. Significant rise in triglyceride level should be considered as indication for dose reduction, drug discontinuation, or combined or alternate therapy.

HOW SUPPLIED

COLESTID Tablets are yellow, elliptical, imprinted U, and are supplied as follows:

Bottles of 120 NDC 0009-0450-03

Each tablet contains 1 gram of micronized colestipol hydrochloride.

Store at controlled room temperature 20° to 25°C (68° to 77°F) [see USP].

REFERENCES

1. Summary of the Second Report of the National Cholesterol Education Program (NCEP) Expert Panel on Detection, Evaluation, and Treatment of High Blood Cholesterol in Adults (Adult Treatment Panel II). JAMA 1993; 269(23):3015–3023.
2. Lipid Metabolism-Atherogenesis Branch, National Heart, Lung, and Blood Institute, Bethesda, MD: The Lipid Research Clinics Coronary Primary Prevention Trial Results. I. Reduction in Incidence of Coronary Heart Disease. JAMA 1984; 251:351–364.
3. Parra HJ, et al. Differential electroimmunoassay of human LpA-I lipoprotein particles on ready-to-use plates. Clin. Chem. 1990; 36(8):1431–1435.
4. Barbaras R, et al. Cholesterol efflux from cultured adipose cells is mediated by LpAI particles but not by LpAI:AII particles. Biochem. Biophys. Res. Comm. 1987; 142(1):63–69.
5. Kane JP, et al. Normalization of low-density-lipoprotein levels in heterozygous familial hypercholesterolemia with a combined drug regimen. N Engl. J. Med. 1981; 304:251–258.
6. Illingworth DR, et al. Colestipol plus nicotinic acid in treatment of heterozygous familial hypercholesterolemia. Lancet 1981; 1:296–298.
7. Kuo PT, et al. Familial type II hyperlipoproteinemia with coronary heart disease: Effect of diet-colestipol-nicotinic acid treatment. Chest 1981; 79:286–291.
8. Blankenhorn DH, et al. Beneficial Effects of Combined Colestipol-Niacin Therapy on Coronary Atherosclerosis and Coronary Venous Bypass Grafts. JAMA 1987; 257(23):3233–3240.
9. Cashin-Hemphill L, et al. Beneficial Effects of Colestipol-Niacin on Coronary Atherosclerosis: A 4-Year Follow-up. JAMA 1990; 264:3013–3017.
10. Brown G. et al. Regression of Coronary Artery Disease as a Result of Intensive Lipid-Lowering Therapy in Men with High Levels of Apolipoprotein B. N. Engl. J. Med. 1990; 323:1289–1298.
11. Kane JP, et al. Regression of Coronary Atherosclerosis During Treatment of Familial Hypercholesterolemia with Combined Drug Regimens. JAMA 1990; 264:3007–3012.

Rx only

LAB-0053-6.0
Revised August 2023

PRINCIPAL DISPLAY PANEL - 1 g Tablet Bottle Label

Pfizer

NDC 0009-0450-03

Colestid®
(colestipol hydrochloride)
tablets

1 g

120 Tablets
Rx only